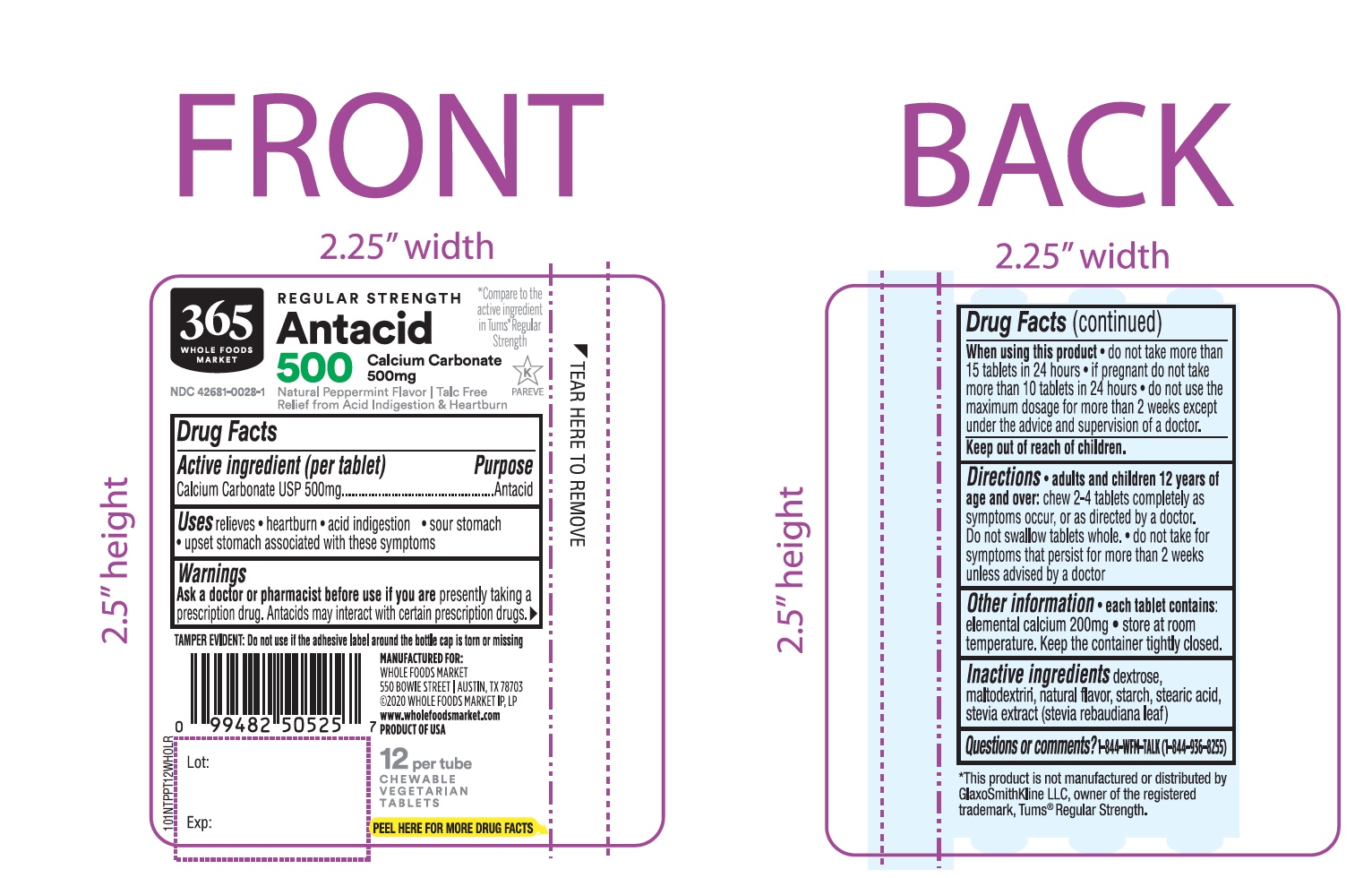 DRUG LABEL: Whole Foods Market Regular Strength

NDC: 42681-0028 | Form: TABLET, CHEWABLE
Manufacturer: WHOLE FOODS MARKET, INC.
Category: otc | Type: HUMAN OTC DRUG LABEL
Date: 20251019

ACTIVE INGREDIENTS: CALCIUM CARBONATE 500 mg/1 1
INACTIVE INGREDIENTS: DEXTROSE, UNSPECIFIED FORM; MALTODEXTRIN; STARCH, CORN; STEARIC ACID; STEVIA REBAUDIANA LEAF

Whole Foods Regular Strength Peppermint Flavor Antacid Drug Facts

Active ingredient (per tablet)

Calcium Carbonate USP 500mg

Purpose

Antacid

Uses

relieves

- heartburn
- acid indigestion
- sour stomach
- upset stomach associated with these symptoms

Warnings

Ask a doctor or pharmacist before use if you are

presently taking a prescription drug. Antacids may interact with certain prescription drugs.

When using this product

- do not take more than 15 tablets in 24 hours
- if pregnant do not take more than 10 tablets in 24 hours
- do not use the maximum dosage for more than 2 weeks except under the advice and supervision of a doctor

Directions

- adults and children 12 years of age and over:chew 2-4 tablets as symptoms occur, or as directed by a doctor. Do not swallow tablets whole.
- do not take for symptoms that persist for more than 2 weeks unless advised by a doctor

Other information

- each tablet contains: elemental calcium 200mg
- store at room temperature. Keep the container tightly closed.

Inactive ingredients

dextrose, maltodextrin, natural flavor, starch, stearic acid, stevia extract (stevia rebaudiana leaf).

Questions or comments?

1-844-WFM-TALK (1-844-936-8255)

SAFETY SEALED: DO NOT USE IF PRINTED SEAL UNDER CAP IS TORN OR MISSING.

Principal Display Panel

WHOLE FOODS MARKET

NDC#42681-0028-1

Compare to the Active Ingredient in Tums®Regular Strength*

REGULAR STRENGTH

Antacid

500

Calcium Carbonate 500mg

Natural Peppermint Flavor

Relief from Heartburn and Acid Indigestion

Talc Free

12 CHEWABLE VEGETERIAN TABLETS per tube

MANUFACTURED FOR:

WHOLE FOODS MARKET

550 BOWIE STREET I AUSTIN, TX 78703

©2020 WHOLE FOODS MARKET IP, LP

www.wholefoodsmarket.com

PRODUCT OF USA

*This product is not manufactured or distributed by GlaxoSmithKline LLC, owner of the registered trademark, Tums®Regular Strength.